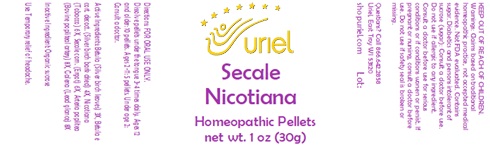 DRUG LABEL: Secale Nicotiana
NDC: 48951-8177 | Form: PELLET
Manufacturer: Uriel Pharmacy Inc.
Category: homeopathic | Type: HUMAN OTC DRUG LABEL
Date: 20231108

ACTIVE INGREDIENTS: BETULA PUBESCENS LEAF 3 [hp_X]/1 1; BETULA PUBESCENS BARK 4 [hp_X]/1 1; TOBACCO LEAF 6 [hp_X]/1 1; CLAVICEPS PURPUREA SCLEROTIUM 6 [hp_X]/1 1; BOS TAURUS ARTERY 8 [hp_X]/1 1; LEAD SULFIDE 8 [hp_X]/1 1
INACTIVE INGREDIENTS: SUCROSE

Secale Nicotiana

INDICATIONS AND USAGE

Directions: FOR ORAL USE ONLY.

DOSAGE AND ADMINISTRATION

Dissolve pellets under the tongue 3-4 times daily. Ages 12 and older: 10 pellets. Ages 2-11: 5 pellets. Under age 2: Consult a doctor.

ACTIVE INGREDIENT

Active Ingredients: Betula (Silver birch leaves) 3X, Betula e cort. decoct. (Silver birch bark dried) 4X, Nicotiana (Tobacco) 6X, Secale corn. (Ergot) 6X, Arteria poplitea (Bovine popliteal artery) 8X, Galena (Lead glance) 8X

Inactive Ingredient: Organic sucrose

PURPOSE

Use: Temporary relief of headache.

KEEP OUT OF REACH OF CHILDREN.

WARNINGS

Warnings: Claims based on traditional homeopathic practice, not accepted medical evidence. Not FDA evaluated. Contains sugar. Diabetics and persons intolerant of sucrose (sugar): Consult a doctor before use. Do not use if allergic to any ingredient. Consult a doctor before use for serious conditions or if conditions worsen or persist. If pregnant or nursing, consult a doctor before use. Do not use if safety seal is broken or missing.

QUESTIONS

Questions? Call 866.642.2858 Uriel, East Troy WI 53120 shopuriel.com